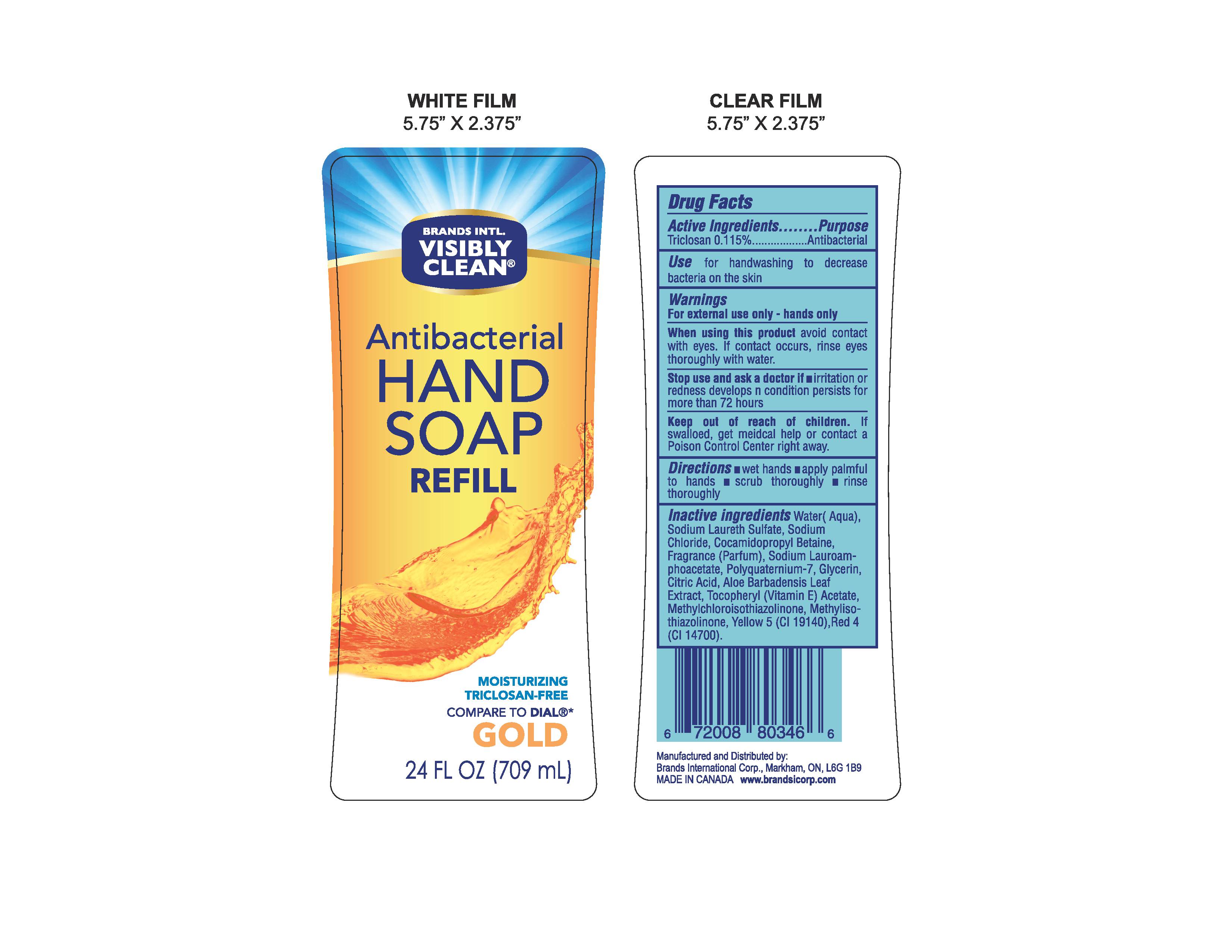 DRUG LABEL: Antibacterial
NDC: 50157-201 | Form: LIQUID
Manufacturer: Brands International Corp
Category: otc | Type: HUMAN OTC DRUG LABEL
Date: 20160506

ACTIVE INGREDIENTS: TRICLOSAN 1.15 mg/100 mL
INACTIVE INGREDIENTS: METHYLISOTHIAZOLINONE; FD&C YELLOW NO. 5; FD&C RED NO. 4; METHYLCHLOROISOTHIAZOLINONE; WATER; SODIUM LAURETH SULFATE; SODIUM CHLORIDE; COCAMIDOPROPYL BETAINE; SODIUM LAUROAMPHOACETATE; POLYQUATERNIUM-7 (70/30 ACRYLAMIDE/DADMAC; 1600 KD); GLYCERIN; ANHYDROUS CITRIC ACID; ALOE VERA LEAF; .ALPHA.-TOCOPHEROL ACETATE, DL-

Active Ingredient - Triclosan 0.115%

Purpose - Antibacterial

INDICATIONS AND USAGE

Use for handwashing to decrease bacteria on the skin

Warnings

For external use only - hands only

When using this product avoid contact with eyes. If contact occurs, rinse eyes thoroughly with water

Stop use and ask a doctor if irritation or redness develops n condition persists for more than 72 hours

Keep out of reach of children If swallowed, get medical help or contact a Poison Control Center right away

Directions

- wet hands
- apply palmful to hands
- scrub thoroughly
- rinse thoroughly

INACTIVE INGREDIENT

Inactive Ingredients - Water (Aqua), Sodium Laureth Sulfate, Sodium Chloride, Cocamidopropyl Betaine, Fragrance (Parfum), Sodium Lauroamphoacetate, Polyquaternium 7, Glycerin, Citric Acid, Aloe Barbadensis Leaf Extract, Tocopheryl (Vitamin E) Acetate, Methylchloroisothiazolinone, Methylisothiazolinone, Yellow 5 (Cl 19140), Red 4 (Cl 14700)